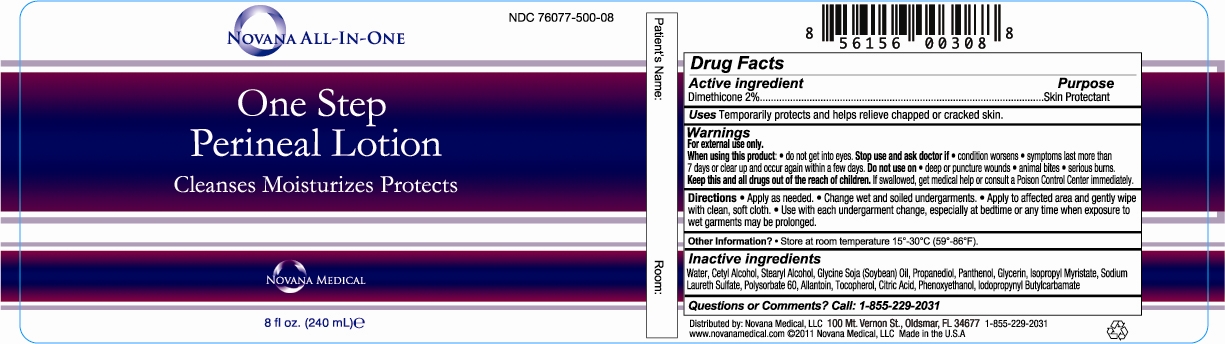 DRUG LABEL: Novana All-In-One One Step Perineal
NDC: 76077-500 | Form: LOTION
Manufacturer: NOVANA MEDICAL LLC
Category: otc | Type: HUMAN OTC DRUG LABEL
Date: 20120404

ACTIVE INGREDIENTS: Dimethicone .02 mL/1 mL
INACTIVE INGREDIENTS: Water; Cetyl Alcohol; Stearyl Alcohol; Soybean Oil; Propanediol; Polysorbate 60; Panthenol; Glycerin; Isopropyl Myristate; Allantoin; Tocopherol; Sodium Laureth Sulfate; CITRIC ACID MONOHYDRATE; Phenoxyethanol; Iodopropynyl Butylcarbamate

Drug Facts

Active ingredient Purpose
Dimethicone 2%.......................................................................................................Skin Protectant

PURPOSE

Uses Temporarily protects and helps relieve chapped or cracked skin.

Warnings
For external use only.
When using this product • Avoid contact with eyes • Stop use and ask doctor if • If condition worsens •symptoms last more than 7 days or clear up and occur again within a few days. Do not use on •deep or puncture wounds •animal bites •serious burns.

KEEP OUT OF REACH OF CHILDREN

Keep this and all drugs out of the reach of children. If swallowed, get medical help or contact a Poison Control Center right away.

DOSAGE AND ADMINISTRATION

For external use only.

INDICATIONS AND USAGE

Directions •Apply as needed. • Change wet and soiled undergarments. • Apply to affected area and gently wipe with clean, soft cloth. • Use with each undergarment change, especially at bedtime or any time when exposure to wet garments may be prolonged.

Inactive ingredients
Water, Cetyl Alcohol, Stearyl Alcohol, Glycine Soja (Soybean) Oil, Propanediol, Polysorbate 60,
Panthenol, Glycerin, Isopropyl Myristate, Allantoin, Tocopherol, Sodium Laureth Sulfate, Citric Acid,
Phenoxyethanol, Iodopropynyl Butylcarbamate